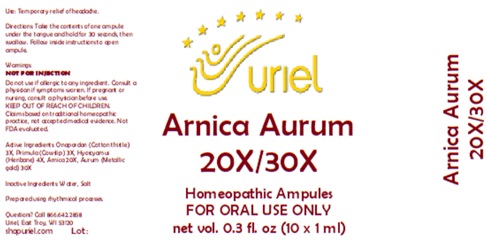 DRUG LABEL: Arnica Aurum 20/30
NDC: 48951-1106 | Form: LIQUID
Manufacturer: Uriel Pharmacy Inc.
Category: homeopathic | Type: HUMAN OTC DRUG LABEL
Date: 20251126

ACTIVE INGREDIENTS: ONOPORDUM ACANTHIUM FLOWER 3 [hp_X]/1 mL; PRIMULA VERIS FLOWER 3 [hp_X]/1 mL; HYOSCYAMUS NIGER LEAF 4 [hp_X]/1 mL; ARNICA MONTANA 20 [hp_X]/1 mL; GOLD 30 [hp_X]/1 mL
INACTIVE INGREDIENTS: WATER; SODIUM CHLORIDE

Arnica Aurum 20/30

PURPOSE

Use: Temporary relief of headache.

INDICATIONS AND USAGE

FOR ORAL USE ONLY

DOSAGE AND ADMINISTRATION

Directions: Take the contents of one ampule under the tongue and hold for 30 seconds, then swallow. Follow inside instructions to open ampule.

Warnings:
NOT FOR INJECTION
Do not use if allergic to any ingredient. Consult a physician if symptoms worsen. If pregnant or nursing, consult a physician before use.
Claims based on traditional homeopathic practice, not accepted medical evidence. Not FDA evaluated.

KEEP OUT OF REACH OF CHILDREN.

ACTIVE INGREDIENT

Active Ingredients: Onopordon (Cotton thistle) 3X, Primula (Cowslip) 3X, Hyoscyamus (Henbane) 4X, Arnica 20X, Aurum (Metallic gold) 30X

Inactive Ingredients: Water, Salt

Prepared using rhythmical processes.

QUESTIONS

Questions? Call 866.642.2858 Uriel, East Troy, WI 53120 shopuriel.com